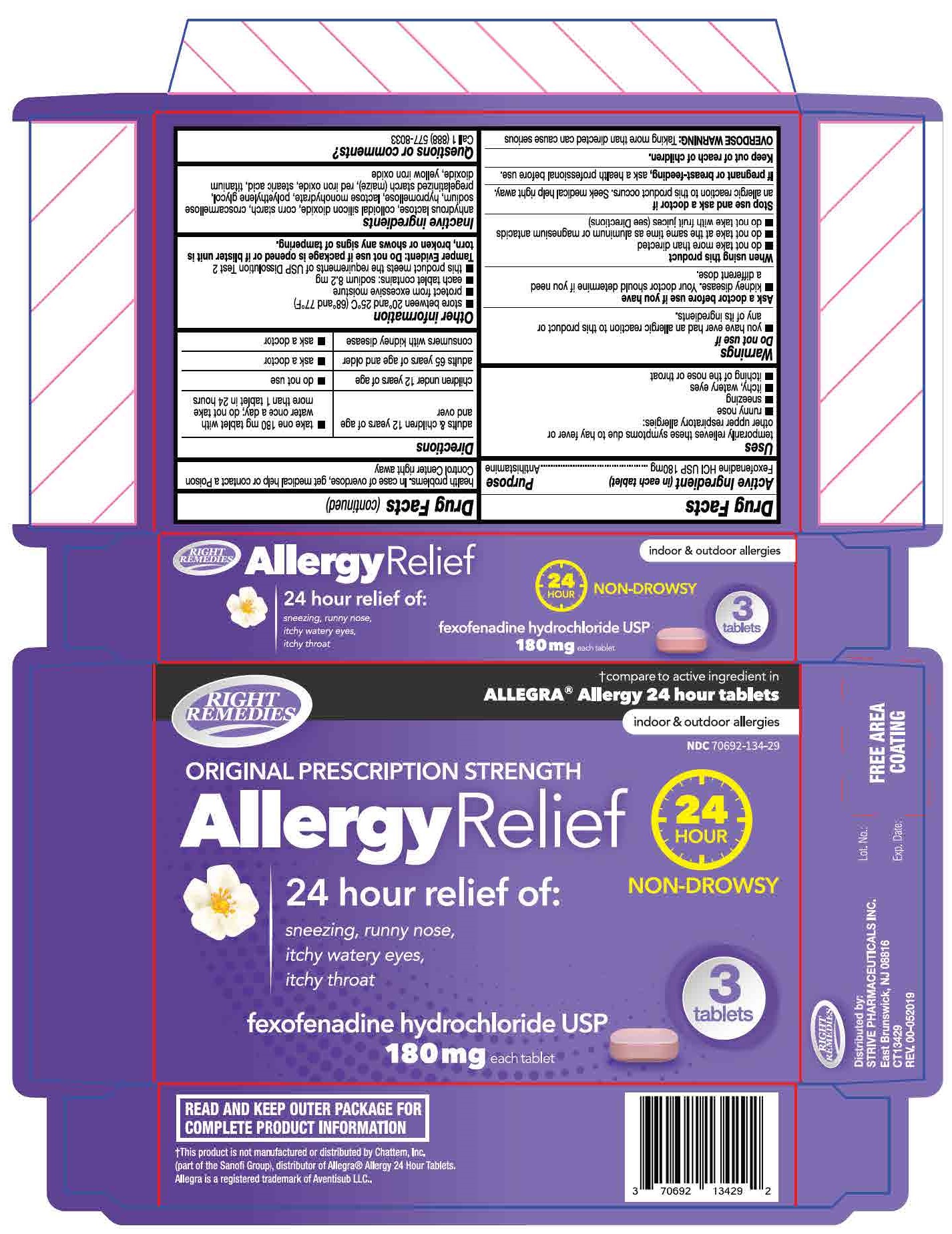 DRUG LABEL: Fexofenadine hydrochloride
NDC: 70692-134 | Form: TABLET
Manufacturer: Strive Pharmaceuticals Inc
Category: otc | Type: HUMAN OTC DRUG LABEL
Date: 20201116

ACTIVE INGREDIENTS: FEXOFENADINE HYDROCHLORIDE 180 mg/1 1
INACTIVE INGREDIENTS: HYPROMELLOSE, UNSPECIFIED; TITANIUM DIOXIDE; POLYETHYLENE GLYCOL 6000; FERRIC OXIDE RED; STEARIC ACID; STARCH, CORN; SILICON DIOXIDE; FERRIC OXIDE YELLOW; LACTOSE MONOHYDRATE; CROSCARMELLOSE SODIUM

Fexofenadine HCl USP 180mg
Allergy Relief - 24 hours

ACTIVE INGREDIENT

Fexofenadine HCl USP 180 mg

INACTIVE INGREDIENT

anhydrous lactose, colloidal silicon dioxide, corn starch, croscarmellose sodium, hypromellose, lactose monohydrate, polyethylene glycol, pregalatinized starch (maize), red iron oxide, stearic acid, titanium dioxide, yellow iron oxide

DOSAGE AND ADMINISTRATION

- adults & children 12 years of age and over: take one 180 mg tablet with water once a day; do not take more than 1 tablet in 24 hours
- children under 12 years of age: do not use
- adults 65 years of age and older: ask a doctor
- consumers with kidney disease: ask a doctor

INDICATIONS AND USAGE

temporarily relieves these symptoms due to hay fever or other respiratory allergies:

- runny nose
- sneezing
- itchy, watery eyes
- itching of the nose or throat

Do not use

- if you have ever had an allergic reaction to this product or any of its ingredients.

Ask a doctor before use if you have

- kidney disease. Your doctor should determine if you need a different dose.

When using this product

- do not take more than directed
- do not take at the same time as aluminum or magnesium antacids
- do not take with fruit juices

Stop use and ask a doctor if

an allergic reaction to this product occurs. Seek medical help right away.

If pregnant or breast-feeding,

ask a health professional before use

Keep out of reach of children

Overdose warning: Taking more than directed can cause serious health problems. In case of overdose, get medical help or contact a Poison Control Center right away.

Keep out of reach of children

Overdose Warning: Taking more than directed can cause serious health problems. Incase of overdose, get medical help or contact a Poison Control Center right away.

PURPOSE

Antihistamine

OTHER SAFETY INFORMATION

- store at room temperature between 20ºC - 25ºC (68ºF - 77ºF)
- protect from excessive moisture
- each tablet contains: sodium 8.2 mg
- this product meets the requirements of USP Dissolution Test 2

Tamper Evident: Do not use if package is opened or if blister unite is torn broken or shows any signs of tampering.